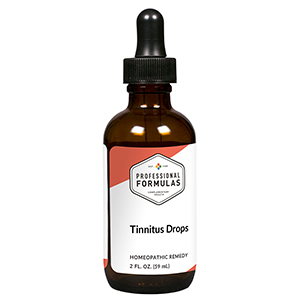 DRUG LABEL: Tinnitus Drops
NDC: 63083-2072 | Form: LIQUID
Manufacturer: Professional Complementary Health Formulas
Category: homeopathic | Type: HUMAN OTC DRUG LABEL
Date: 20190815

ACTIVE INGREDIENTS: BLACK COHOSH 1 [hp_X]/59 mL; GINKGO 1 [hp_X]/59 mL; CINCHONA OFFICINALIS BARK 3 [hp_X]/59 mL; GOLDENSEAL 5 [hp_X]/59 mL; SUS SCROFA EAR 6 [hp_X]/59 mL; LYCOPODIUM CLAVATUM SPORE 6 [hp_X]/59 mL; BOS TAURUS NERVE 6 [hp_X]/59 mL; SULFUR 6 [hp_X]/59 mL; DIGITALIS 12 [hp_X]/59 mL; POTASSIUM CARBONATE 30 [hp_X]/59 mL
INACTIVE INGREDIENTS: ALCOHOL; WATER

C72

ACTIVE INGREDIENTS

Cimicifuga racemosa 1X
Ginkgo biloba 1X
Cinchona officinalis 3X, 6X, 12X, 30X
Hydrastis canadensis 5X
Ear 6X, 12X, 30X
Lycopodium clavatum 6X, 12X
Major nerves 6X, 12X, 30X
Sulphur 6X, 12X
Digitalis purpurea 12X
Kali carbonicum 30X

QUESTIONS

Professional Formulas

PO Box 2034 Lake Oswego, OR 97035

INDICATIONS

For the temporary relief of noise in the ears, such as ringing, roaring, buzzing, hissing, or whistling.*

PURPOSE

*Claims based on traditional homeopathic practice, not accepted medical evidence. Not FDA evaluated.

WARNINGS

Persistent symptoms may be a sign of a serious condition. If symptoms persist or are accompanied by a fever, persistent headache, dizziness, or loss of hearing, consult a doctor. Keep out of the reach of children. In case of overdose, get medical help or contact a poison control center right away. If pregnant or breastfeeding, ask a healthcare professional before use.

Keep out of the reach of children.

PREGNANCY OR BREAST FEEDING

If pregnant or breastfeeding, ask a healthcare professional before use.

DIRECTIONS

Place drops under tongue 30 minutes before/after meals. Adults and children 12 years and over: Take 10 drops up to 3 times per day for up to 6 weeks. For immediate onset of symptoms, take 10 to 15 drops every 15 minutes up to 3 hours. For less severe symptoms, take 10-15 drops hourly up to 8 hours. Consult a physician for use in children under 12 years of age.

OTHER INFORMATION

Tamper resistant. If seal is broken, do not use. After opening, close container tightly and store at room temperature away from heat.

INACTIVE INGREDIENTS

20% ethanol, purified water.

LABEL

Est 1985

Professional Formulas

Complementary Health

Tinnitus Drops

Homeopathic Remedy

2 FL. OZ. (59 mL)